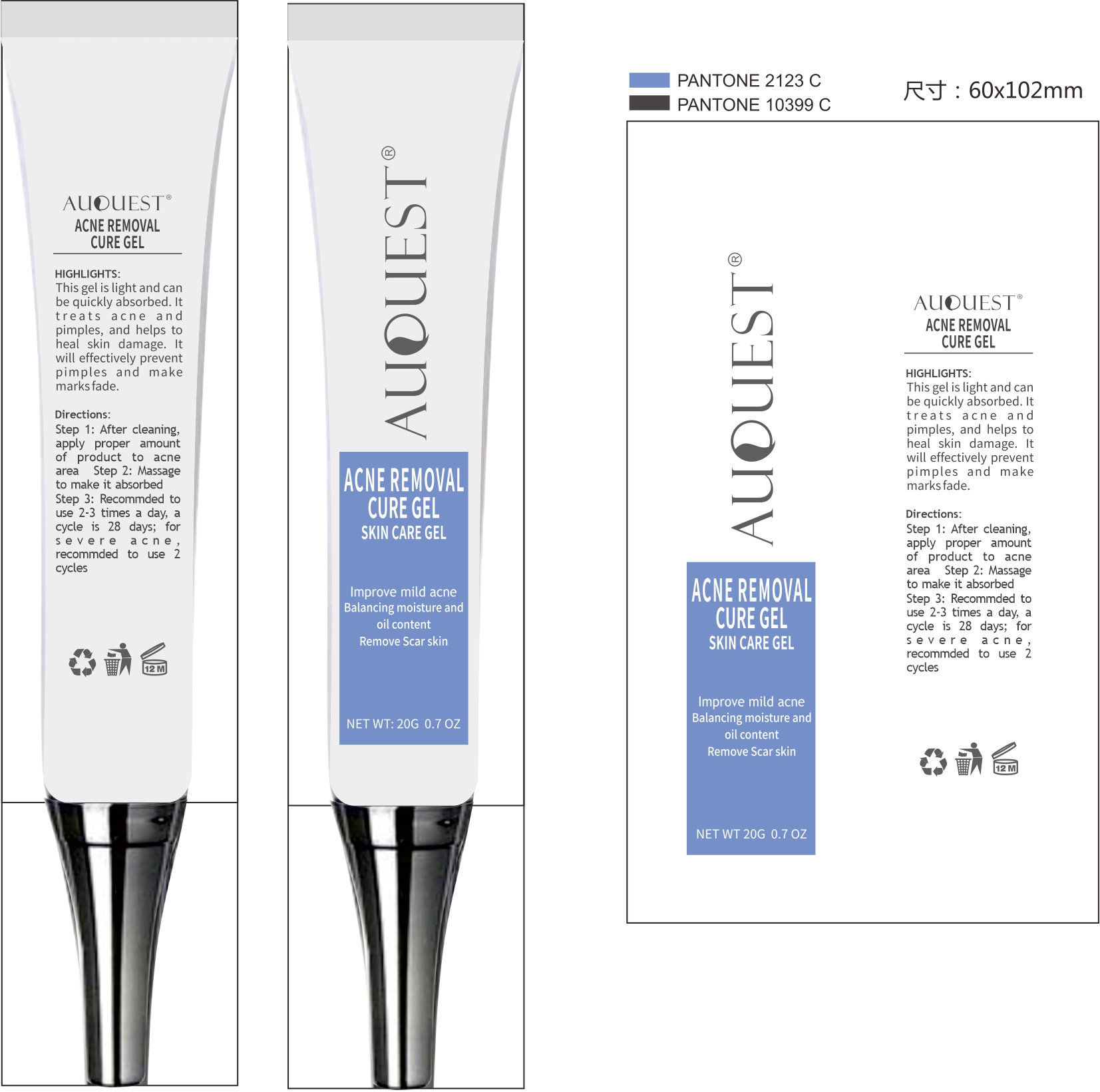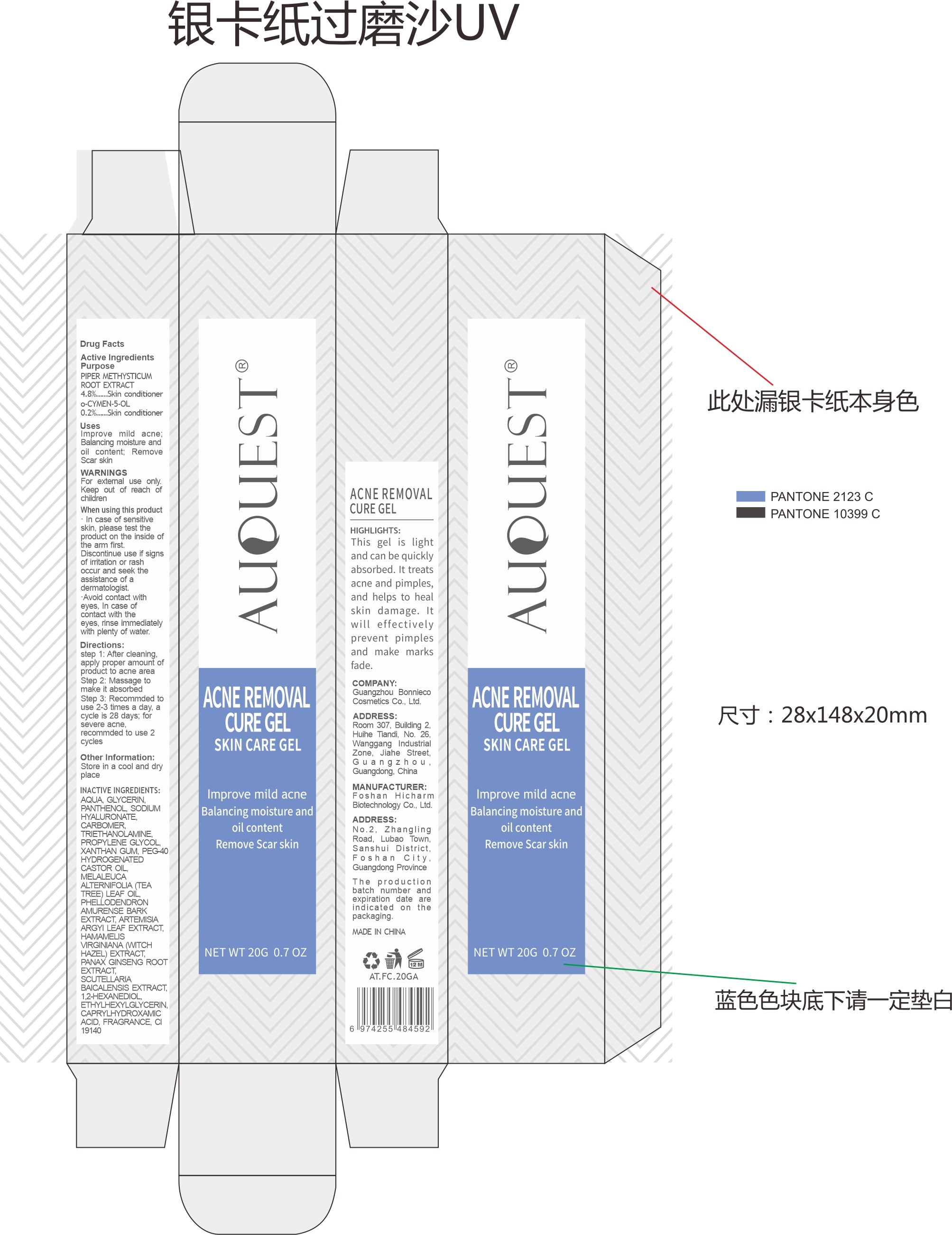 DRUG LABEL: Auquest Acne Removal Cure Gel Skin Care Gel
NDC: 84186-017 | Form: CREAM
Manufacturer: Guangzhou Bonnieco Cosmetics Co., Ltd
Category: otc | Type: HUMAN OTC DRUG LABEL
Date: 20240528

ACTIVE INGREDIENTS: GLYCERIN 5 g/100 g
INACTIVE INGREDIENTS: CARBOMER HOMOPOLYMER, UNSPECIFIED TYPE; TROLAMINE; PROPYLENE; ETHYLENE GLYCOL; ETHYLHEXYLGLYCERIN; FRAGRANCE 13576; XANTHAN GUM; PHELLODENDRON CHINENSE WHOLE; PEG-40 HYDROGENATED LANOLIN; CASTOR OIL; FD&C YELLOW NO. 5; PANTHENOL; (-)-DEHYDROGRISEOFULVIN; MELALEUCA VIRIDIFLORA WHOLE; CANOLA OIL; WATER; HYALURONATE SODIUM; PREMNA SERRATIFOLIA LEAF; BETA-ADRENERGIC RECEPTOR KINASE 1; ARTEMISIA MONGOLICA WHOLE; CAPRYLHYDROXAMIC ACID

84186-017

Active Ingredient

GLYCERIN 5%

Purpose

face (body part)

Use

lmprove mild acne: Balancing moisture and oil content; Remove Scar skin

Warnings

For extemal use only. Keep out of reach of children When using this product In case of sensitive skin, please test the product on the inside of the amm first. Discontinue use if signs of irritation or rash occur and seek the assistance of a dermatologist. Avoid contact with eyes, In case of contact with the eyes, rinse immediately with plenty of water.

Do not use

This gel is light and can be quickly absorbed. lt treats acne and pimples, and helps to heal skin damage. Lt will effectively prevent pimples and make marks fade.

When Using

In case of contact with the eyes, rinse immediately with plenty of water.

Stop Use

If discomfort arises, please immediately stop using the product and seek the assistance of a dermatologist.

Ask Doctor

If discomfort arises, please immediately stop using the product and seek the assistance of a dermatologist.

Keep Oot Of Reach Of Children

Directions

step 1: After cleaning. apply proper amount of product to acne area
Step 2: Massage to make it absorbed
Step 3: Recommded to use 2-3 times a day, a cycle is 28 days; for severe acne
recommded to use 2 cycles

Inactive ingredients

AQUA, GLYCERIN. PANTHENOL SODIUM HYALURONATE CARBOMER, TRIETHANOLAMINE. PROPYLENE GLYCOL XANTHAN GUM, PEG-40 HYDROGENATED CASTOR OIL, MELALEUCA ALTERNIFOLIA (TEA TREE) LEAF OIL PHELLODENDRON AMURENSE BARK EXTRACT ARTEMISIA ARGYI LEAF EXTRACT HAMAMELIS VRGINIANA (ITCHHAZEL)EXTRACT PANAX GINSENG ROOT EXTRACT SCUTELLARIA BAICALENSIS EXTRACT, 1.2-HEXANEDIOL ETHYLHEXYLGLYCERIN CAPRYLHYDROXAMIC ACID,FRAGRANCE.CI19140